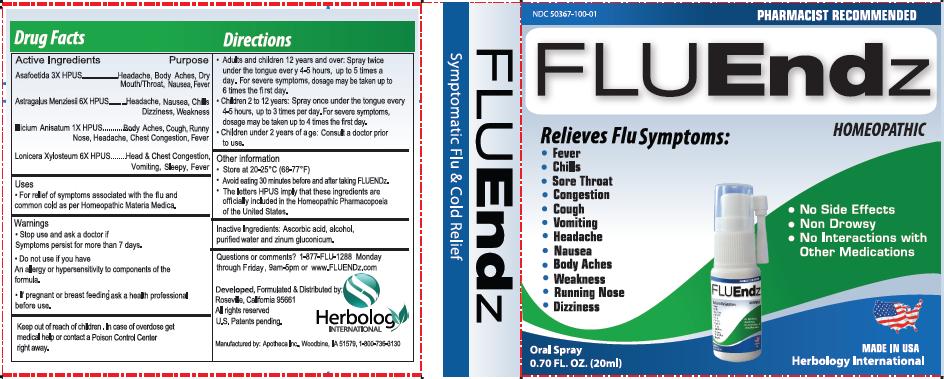 DRUG LABEL: FLUEndz
NDC: 50367-100 | Form: SPRAY
Manufacturer: Herbology International LLC
Category: homeopathic | Type: HUMAN OTC DRUG LABEL
Date: 20100208

ACTIVE INGREDIENTS: ASAFETIDA 3 [hp_X]/20 mL; ASTRAGALUS NUTTALLII LEAF 6 [hp_X]/20 mL; STAR ANISE 1 [hp_X]/20 mL; LONICERA XYLOSTEUM FRUIT 6 [hp_X]/20 mL

INDICATIONS AND USAGE

- For relief of symptoms associated with the flu and common cold as per Homeopathic Materia Medica.

INACTIVE INGREDIENT

Inactive Ingredients: Ascorbic acid, alcohol, purified water and zinum gluconicum

DOSAGE AND ADMINISTRATION

- Adults and children 12 years and over: Spray twice under the tongue every 4-5 hours, up to 5 times a day. For severe symptoms, dosage may be taken up to 6 times the first day.
- Children 2 to 12 years: Spray once under the tongue every 4-5 hours, up to 3 times per day. For severe symptoms, dosage may be taken up to 4 times the first day.
- Children under 2 years of age: Consult a doctor prior to use.

Warnings:

- Stop use and ask a doctor if symptoms persist for more than 7 days.
- Do not use if you have an allergy or hypersensitivity to components of the formula.
- If pregnant or breast feeding ask a health professional before use.
- Keep out of reach of children. In case of overdose, get medical help or contact a Poison Control Center right away.

PACKAGE LABEL

- No Side Effects
- Non Drowsy
- No Interactions with Other Medications

Relieves Flu Symptoms:

- Fever
- Chills
- Sore Throat
- Congestion
- Cough
- Vomiting
- Headache
- Nausea
- Body Aches
- Weakness
- Running Nose
- Dizziness

Questions or Comments? 1-877-FLU-1288 Monday through Friday, 9am-5pm or www.FLUEndz.com

Developed, Formulated and Distributed by:
Herbology International
Roseville, California 95661
All rights reserved
U.S. Patents Pending

Manufactured by: Apotheca Inc., Woodbine, IA 51579, 1-800-736-3130

Other Information

- Store at 20-25 degrees C (68-77 degrees F)
- Avoid eating 30 minutes before and after taking FLUEndz
- The letters HPUS imply that these ingredients are officially included in the Homeopathic Pharmacopoeia of the United States